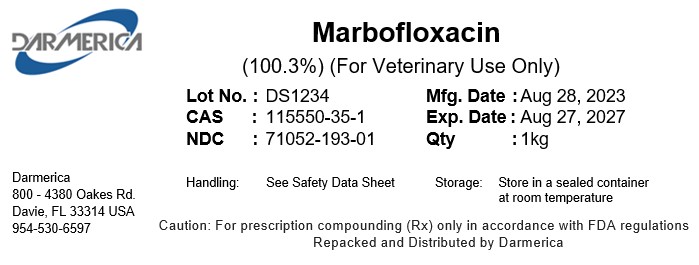 DRUG LABEL: Marbofloxacin
NDC: 71052-193 | Form: POWDER
Manufacturer: DARMERICA, LLC
Category: other | Type: BULK INGREDIENT - ANIMAL DRUG
Date: 20241206

ACTIVE INGREDIENTS: Marbofloxacin 1 kg/1 kg

Marbofloxacin